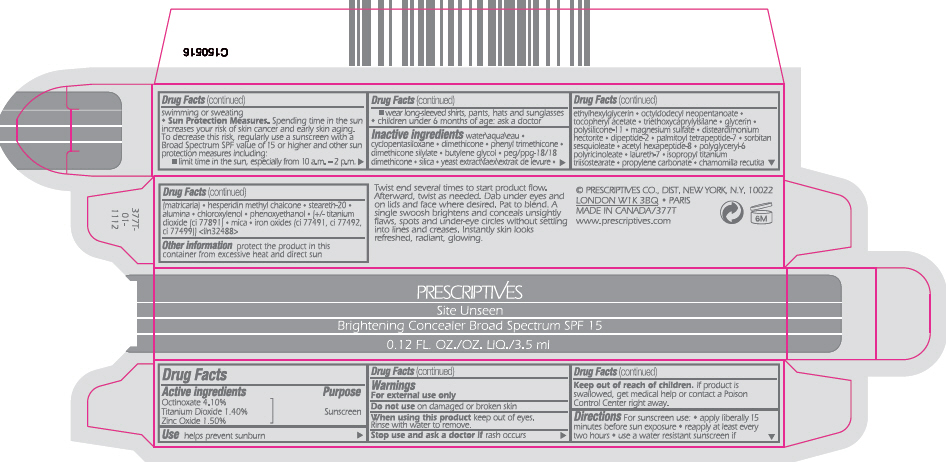 DRUG LABEL: PRESCRIPTIVES 
NDC: 59158-913 | Form: LIQUID
Manufacturer: PRESCRIPTIVES INC.
Category: otc | Type: HUMAN OTC DRUG LABEL
Date: 20121115

ACTIVE INGREDIENTS: OCTINOXATE .04551 g/1 mL; TITANIUM DIOXIDE .01554 g/1 mL; ZINC OXIDE 0.01665 g/1 mL
INACTIVE INGREDIENTS: WATER; CYCLOMETHICONE 5; DIMETHICONE; PHENYL TRIMETHICONE; BUTYLENE GLYCOL; PEG/PPG-18/18 DIMETHICONE; SILICON DIOXIDE; YEAST; ETHYLHEXYLGLYCERIN; OCTYLDODECYL NEOPENTANOATE; .ALPHA.-TOCOPHEROL ACETATE; TRIETHOXYCAPRYLYLSILANE; GLYCERIN; MAGNESIUM SULFATE; VALYLTRYPTOPHAN; PALMITOYL TETRAPEPTIDE-7; SORBITAN SESQUIOLEATE; ACETYL HEXAPEPTIDE-8; LAURETH-7; ISOPROPYL TITANIUM TRIISOSTEARATE; PROPYLENE CARBONATE; MATRICARIA RECUTITA; HESPERIDIN METHYLCHALCONE; STEARETH-20; ALUMINUM OXIDE; CHLOROXYLENOL; PHENOXYETHANOL; MICA; FERRIC OXIDE RED; FERRIC OXIDE YELLOW; FERROSOFERRIC OXIDE

PRESCRIPTIVES
Site Unseen Brightening Concealer Broad Spectrum SPF 15

Drug Facts

Active ingredients

Octinoxate 4.10%
Titanium Dioxide 1.40%
Zinc Oxide 1.50%

Purpose

Sunscreen

Use

helps prevent sunburn

Warnings

For external use only

Do not use on damaged or broken skin

When using this product keep out of eyes. Rinse with water to remove.

Stop use and ask a doctor if rash occurs

Keep out of reach of children. If product is swallowed, get medical help or contact a Poison Control Center right away.

Directions

For sunscreen use:

- apply liberally 15 minutes before sun exposure
- reapply at least every two hours
- use a water resistant sunscreen if swimming or sweating
- Sun Protection Measures. Spending time in the sun increases your risk of skin cancer and early skin aging. To decrease this risk, regularly use a sunscreen with a Broad Spectrum SPF value of 15 or higher and other sun protection measures including:
  - limit time in the sun, especially from 10 a.m. – 2 p.m.
  - wear long-sleeved shirts, pants, hats and sunglasses
- children under 6 months of age: ask a doctor

Inactive ingredients

water\aqua\eau • cyclopentasiloxane • dimethicone • phenyl trimethicone • dimethicone silylate • butylene glycol • peg/ppg-18/18 dimethicone • silica • yeast extract\faex\extrait de levure • ethylhexylglycerin • octyldodecyl neopentanoate • tocopheryl acetate • triethoxycaprylylsilane • glycerin • polysilicone-11 • magnesium sulfate • disteardimonium hectorite • dipeptide-2 • palmitoyl tetrapeptide-7 • sorbitan sesquioleate • acetyl hexapeptide-8 • polyglyceryl-6 polyricinoleate • laureth-7 • isopropyl titanium triisostearate • propylene carbonate • chamomilla recutita (matricaria) • hesperidin methyl chalcone • steareth-20 • alumina • chloroxylenol • phenoxyethanol • [+/- titanium dioxide (ci 77891) • mica • iron oxides (ci 77491, ci 77492, ci 77499)] <iln32488>

Other information

protect the product in this container from excessive heat and direct sun

DIST. NEW YORK, N.Y. 10022

PRINCIPAL DISPLAY PANEL - 3.5 ml Carton

PRESCRIPTIVES
Site Unseen
Brightening Concealer Broad Spectrum SPF 15
0.12 FL. OZ./OZ. LIQ./3.5 ml